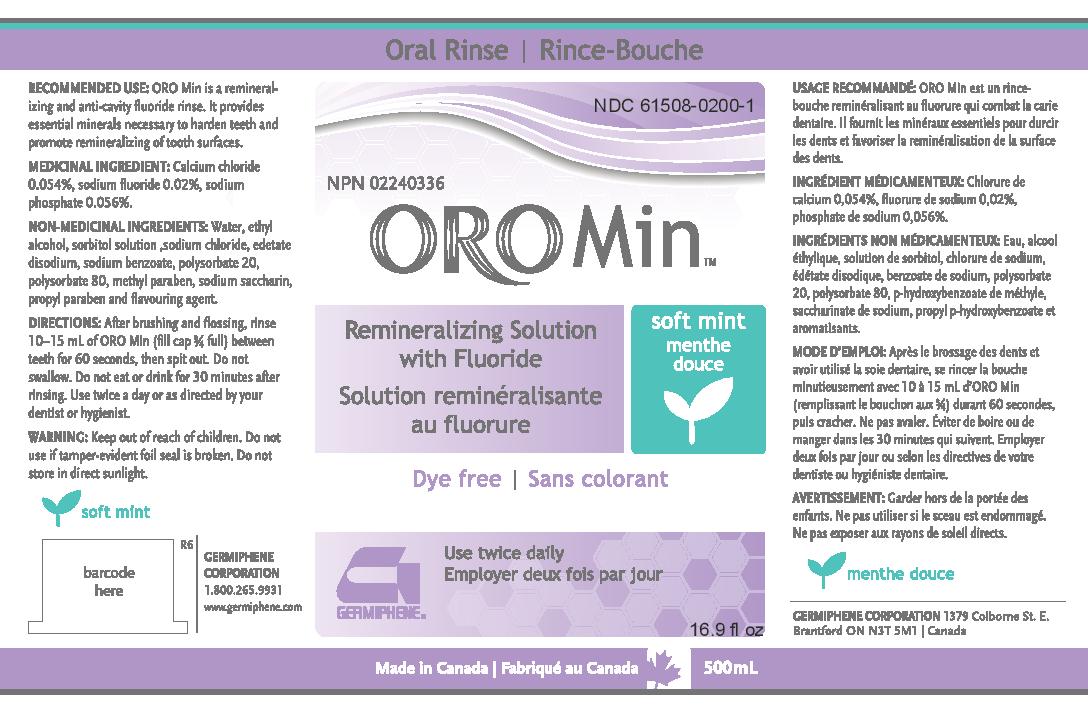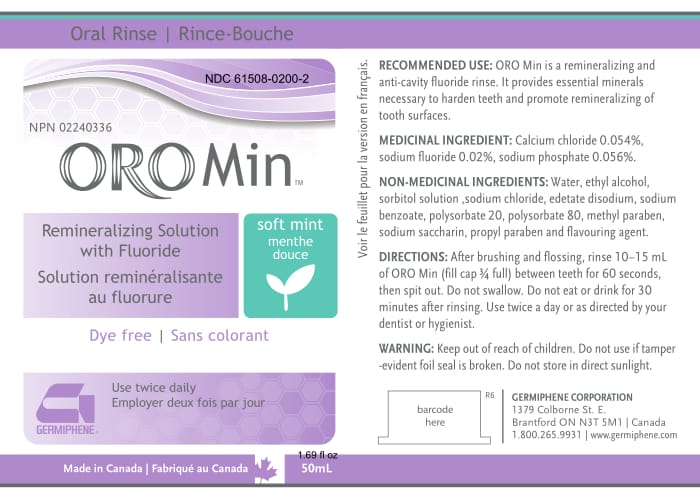 DRUG LABEL: OroMin
NDC: 61508-0200 | Form: RINSE
Manufacturer: Germiphene Corporation
Category: otc | Type: HUMAN OTC DRUG LABEL
Date: 20170613

ACTIVE INGREDIENTS: SODIUM PHOSPHATE, MONOBASIC 0.056 g/100 g; CALCIUM CHLORIDE 0.054 g/100 g; SODIUM FLUORIDE 0.01 g/100 g
INACTIVE INGREDIENTS: ALCOHOL 2 g/100 g; PROPYLPARABEN 0.005 g/100 g; METHYLPARABEN 0.06 g/100 g; DISODIUM ETHYLENEDIAMINEDIACETATE 0.137 g/100 g; SODIUM CHLORIDE 0.877 g/100 g; SACCHARIN SODIUM 0.025 g/100 g; WATER 94.9 g/100 g; SORBITOL 1.5 g/100 g; POLYSORBATE 80 0.1 g/100 g; POLYSORBATE 20 0.1 g/100 g; SODIUM BENZOATE 0.1 g/100 g

ORO Min

Recommended use:

Oro Min is a remineralizing and anti-cavity fluoride rinse. It provides essential minerals necessary to harden teeth and promote remineralizing of tooth surfaces.

PURPOSE

ORO Min is a remineralizing and anti-cavity fluoride rinse. It provides essential minerals necessary to harden teeth and promote remineralizing of tooth surfaces.

Medicinal ingredient:

Calcium chloride 0.054%, sodium fluoride 0.02%, sodium phosphate 0.056%

Non-Medicinal Ingredients:

Water, ethyl alcohol, sorbitol solution, sodium chloride, edetate disodium, sodium benzoate, polysorbate 20, polysorbate 80, methyl paraben, sodium saccharin, propyl paraben, and flavouring agent.

Directions:

After brushing and flossing, rinse 10-15 mL of ORO Min (fill cap 3/4 full) between teeth for 60 seconds, then spit out. Do not swallow. Do not eat or drink for 30 minutes after rinsing. Use twice a day or as directed by your dentist or hygienist.

Keep out of reach of children.

Do not use if tamper-evident foil seal is broken. Do not store in direct sunlight.